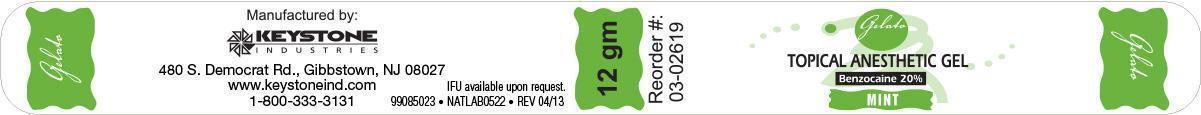 DRUG LABEL: Gelato Topical Anesthetic
NDC: 68400-503 | Form: GEL
Manufacturer: Mycone Dental Supply Co., Inc DBA Keystone Industries and Deepak Products Inc.
Category: prescription | Type: HUMAN PRESCRIPTION DRUG LABEL
Date: 20131226

ACTIVE INGREDIENTS: Benzocaine 2.4 g/12 g
INACTIVE INGREDIENTS: Polyethylene Glycol 400; Polyethylene Glycol 3350; Saccharin Sodium

IFU available upon request.